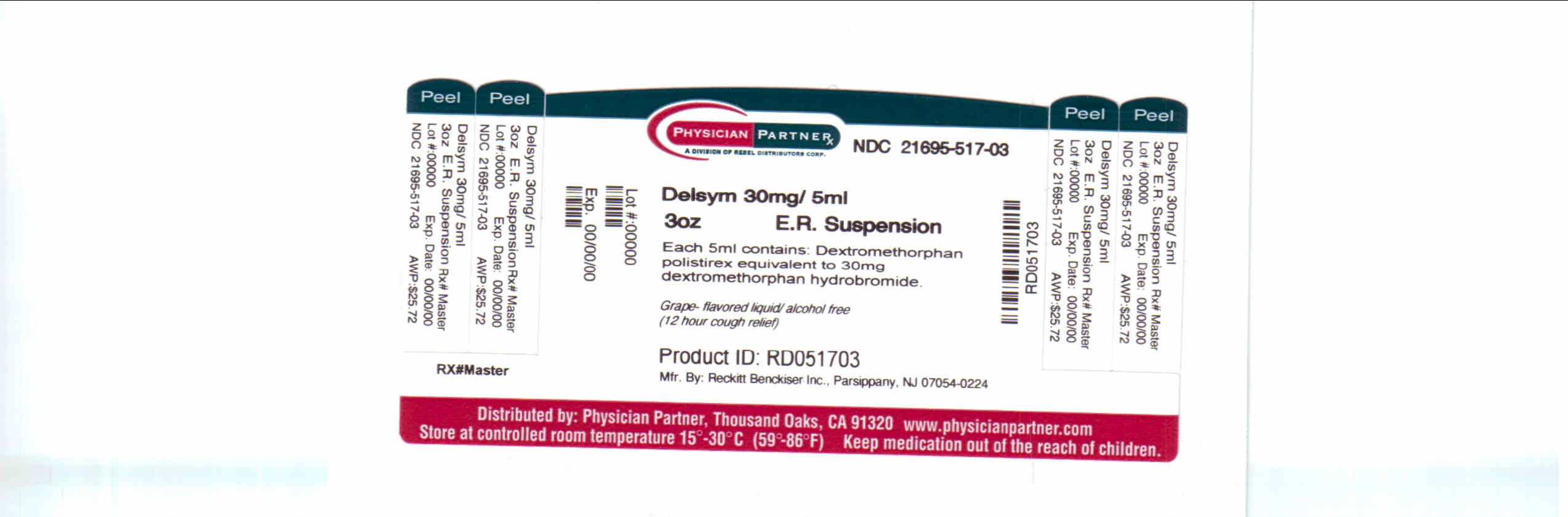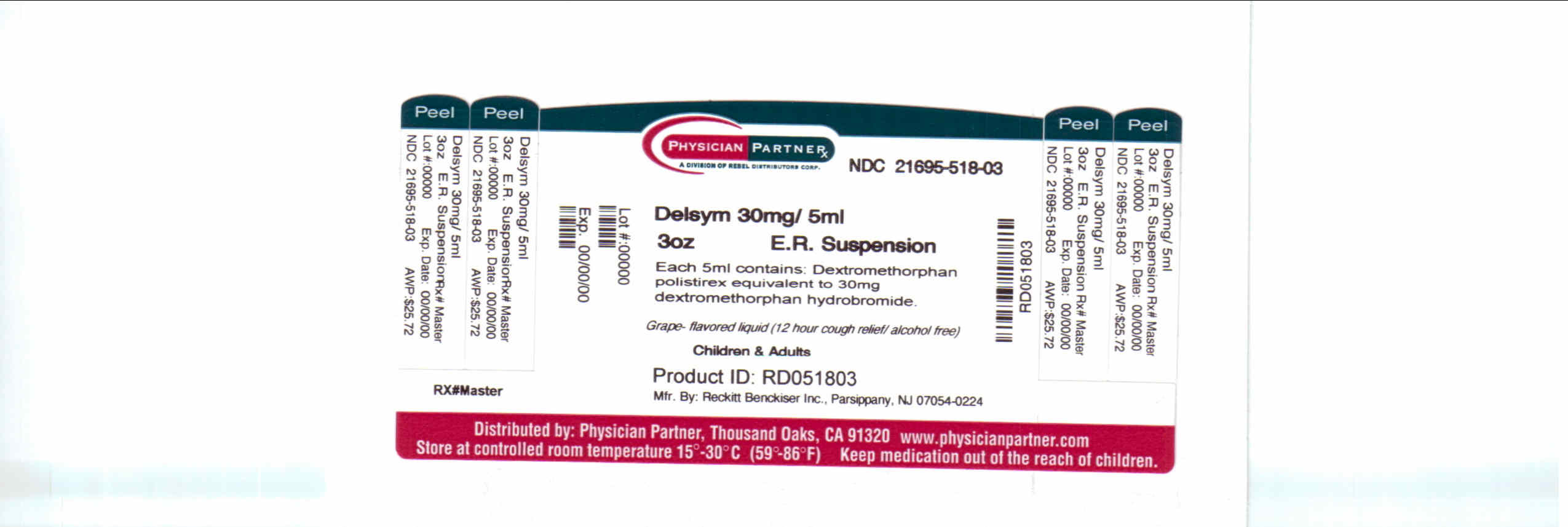 DRUG LABEL: Delsym
NDC: 21695-517 | Form: SYRUP
Manufacturer: Rebel Distributors Corp
Category: otc | Type: HUMAN OTC DRUG LABEL
Date: 20110112

ACTIVE INGREDIENTS: DEXTROMETHORPHAN 30 mg/5 mL
INACTIVE INGREDIENTS: CITRIC ACID MONOHYDRATE; D&C RED NO. 33; EDETATE DISODIUM; ETHYLCELLULOSES; FD&C BLUE NO. 1; HIGH FRUCTOSE CORN SYRUP; METHYLPARABEN; POLYETHYLENE GLYCOL 3350; POLYSORBATE 80; PROPYLENE GLYCOL; PROPYLPARABEN; WATER; SUCROSE; TRAGACANTH; CORN OIL; XANTHAN GUM

Drug Facts

Active ingredient

Dextromethorphan Polistirex

Purpose

Use(s)

temporarily relieves

• cough due to minor throat and bronchial irritation as may occur with the common cold or inhaled irritants

• the impulse to cough to help you get to sleep

Uses

Use(s)

temporarily relieves

• cough due to minor throat and bronchial irritation as may occur with the common cold or inhaled irritants

• the impulse to cough to help you get to sleep

Warnings

Do not use

Do not use if you are now taking a prescription monoamine oxidase inhibitor (MAOI) (certain drugs for depression, psychiatric or emotional conditions, or Parkinson's disease), or for 2 weeks after stopping the MAOI

drug. If you do not know if your prescription drug contains an MAOI, ask a doctor or pharmacist before taking this product.

Ask a doctor before use if you have

• chronic cough that lasts as occurs with smoking, asthma or emphysema

• cough that occurs with too much phlegm (mucus)

Ask a doctor or pharmacist before use if you are

When using this product

Stop use and ask a doctor if

Stop use and ask a doctor if cough lasts more than 7 days, cough comes back, or occurs with fever, rash or headache that lasts. These could be signs of a serious condition.

If pregnant or breast-feeding

Keep out of reach of children

Keep out of reach of children. In case of overdose, get medical help or contact a Poison Control Center right away.

Directions

• shake bottle well before use

• measure only with dosing cup provided. Do not use dosing cup with other products.

• dose as follows or as directed by a doctor

adults and children 12 years of age and over

10 mL every 12 hours,

not to exceed 20 mL in 24 hours

children 6 to under 12 years of age

5 mL every 12 hours,

not to exceed 10 mL in 24 hours

children 4 to under 6 years of age

2.5 mL every 12 hours,

not to exceed 5 mL in 24 hours

children under 4 years of age do not use

Other information

• each 5 mL contains: sodium 7 mg

• store at 20°-25°C (68°-77°F)

• dosing cup provided

Drug Facts

Distributed by: Reckitt Benckiser Inc., Parsippany, NJ 07054-0224 ©RBI 2009

Inactive ingredients

citric acid anhydrous, D&C Red #33, edetate disodium, ethylcellulose, FD&C Blue #1, flavor, high fructose corn syrup, methylparaben, polyethylene glycol 3350, polysorbate 80, propylene glycol, propylparaben,

purified water, sucrose, tragacanth, vegetable oil, xanthan gum